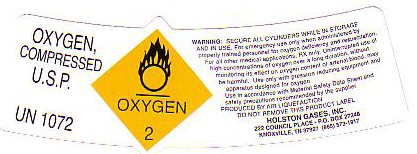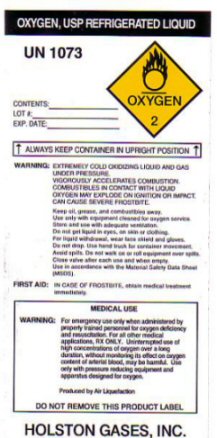 DRUG LABEL: OXYGEN
NDC: 55050-0001 | Form: GAS
Manufacturer: Holston Gases, Inc
Category: prescription | Type: HUMAN PRESCRIPTION DRUG LABEL
Date: 20111024

ACTIVE INGREDIENTS: OXYGEN 99 L/100 L

OXYGEN COMPRESSED LABEL

OXYGEN COMPRESSED U.S.P. UN 1072 - OXYGEN - 2 - WARNING: SECURE ALL CYLINDERS WHILE IN STORAGE AND IN USE. USE IN ACCORDANCE WITH MATERIAL SAFETY DATA SHEET AND SAFETY PRECAUTIONS RECOMMENDED BY THE SUPPLIER. DO NOT REMOVE THIS PRODUCT LABEL.

OXYGEN REFRIGERATED LIQUID LABEL

OXYGEN, USP REFRIGERATED LIQUID UN 1073 OXYGEN - 2

CONTENTS:________________ LOT #:___________________ EXP. DATE: ______________________ ALWAYS KEEP CONTAINER IN UPRIGHT POSITION. WARNING: EXTREMELY COLD OXIDIZING LIQUID AND GAS UNDER PRESSURE. VIGOROUSLY ACCELERATED COMBUSTION. COMBUSTIBLES IN CONTACT WITH LIQUID OXYGEN MAY EXPLODE ON IGNITION OR IMPACT. CAN CAUSE SEVERE FROSTBITE.

KEEP OIL GREASE AND COMBUSTIBLES AWAY. USE ONLY WITH EQUIPMENT CLEANED FOR OXYGEN SERVICE. STORE AND USE WITH ADEQUATE VENTILATION. DO NOT GET LIQUID IN EYES, ON SKIN OR CLOTHING. FOR LIQUID WITHDRAWAL, WEAR FACE SHIELD AND GLOVES. DO NOT DROP. USE HAND TRUCK FOR CONTAINER MOVEMENT. AVOID SPILLS. DO NOT WALK ON OR ROLL EQUIPMENT OVER SPILLS. CLOSE VALVE AFTER EACH USE AND WHEN EMPTY. USE IN ACCORDANCE WITH MATERIAL SAFETY DATA SHEET (MSDS). FIRST AID: IN CASE OF FROSTBITE OBTAIN MEDICAL TREATMENT IMMEDIATELY.

DO NOT REMOVE THIS PRODUCT LABEL.

GENERAL WARNINGS AND PRECAUTIONS

FOR EMERGENCY USE ONLY WHEN ADMINISTERED BY PROPERLY TRAINED PERSONNEL FOR OXYGEN DEFICIENCY AND RESUSCITATION. FOR ALL OTHER MEDICAL APPLICATIONS Rx ONLY. UNINTERRUPTED USE OF HIGH CONCENTRATIONS OF OXYGEN OVER A LONG DURATION, WITHOUT MONITORING ITS EFFECT ON OXYGEN CONTENT OF ARTERIAL BLOOD MAY BE HARMFUL. USE ONLY WITH PRESSURE REDUCING EQUIPMENT AND APPARATUS DESIGNED FOR OXYGEN. PRODUCED BY AIR LIQUEFACTION.